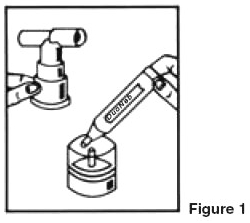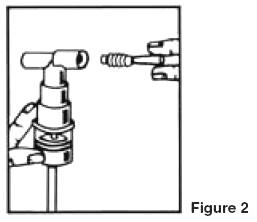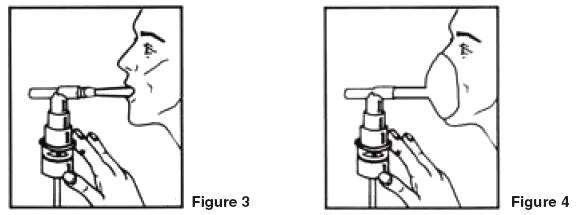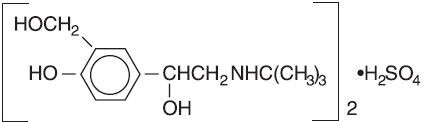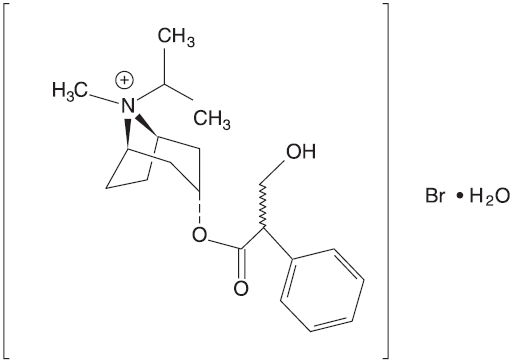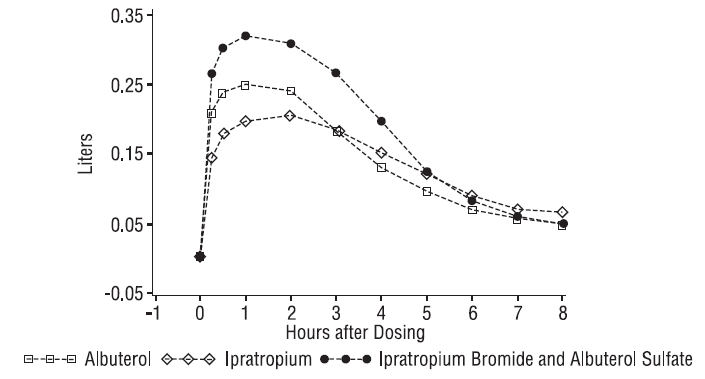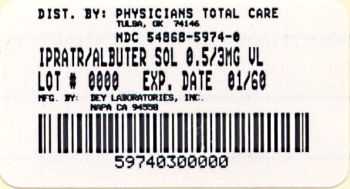 DRUG LABEL: Ipratropium Bromide and Albuterol Sulfate
NDC: 54868-5974 | Form: SOLUTION
Manufacturer: Physicians Total Care, Inc.
Category: prescription | Type: HUMAN PRESCRIPTION DRUG LABEL
Date: 20101105

ACTIVE INGREDIENTS: IPRATROPIUM BROMIDE 0.5 mg/1 1; ALBUTEROL SULFATE 3 mg/1 1
INACTIVE INGREDIENTS: SODIUM CHLORIDE; EDETATE DISODIUM; HYDROCHLORIC ACID

DESCRIPTION

The active components are albuterol sulfate and ipratropium bromide.

Albuterol sulfate, is a salt of racemic albuterol and a relatively selective β2-adrenergic bronchodilator chemically described as α^1-[(tert-butylamino)methyl]-4-hydroxy-m-xylene-α, α’-diol sulfate (2:1) (salt). It has a molecular weight of 576.7 and the empirical formula is (C13H21NO3)2•H2SO4. It is a white crystalline powder, soluble in water and slightly soluble in ethanol. The World Health Organization recommended name for albuterol base is salbutamol.

Figure 3.1-1. Chemical structure of albuterol sulfate.

Ipratropium bromide is an anticholinergic bronchodilator chemically described as 8-azoniabicyclo [3.2.1]-octane, 3-(3-hydroxy-1-oxo-2-phenylpropoxy)-8methyl-8-(1-methylethyl)-, bromide, monohydrate (endo, syn)-, (±)-; a synthetic quaternary ammonium compound, chemically related to atropine. It has a molecular weight of 430.4 and the empirical formula is C20H30BrNO3•H2O. It is a white crystalline substance, freely soluble in water and lower alcohols, and insoluble in lipophilic solvents such as ether, chloroform, and fluorocarbons.

Figure 3.1-2. Chemical structure of ipratropium bromide.

Each 3 mL vial of Ipratropium Bromide and Albuterol Sulfate contains 3.0 mg (0.1%) of albuterol sulfate (equivalent to 2.5 mg (0.083%) of albuterol base) and 0.5 mg (0.017%) of ipratropium bromide in an isotonic, sterile, aqueous solution containing sodium chloride, hydrochloric acid to adjust to pH 4, and edetate disodium, USP (a chelating agent).

Ipratropium Bromide and Albuterol Sulfate is a clear, colorless solution. It does not require dilution prior to administration by nebulization. For Ipratropium Bromide and Albuterol Sulfate Inhalation Solution, like all other nebulized treatments, the amount delivered to the lungs will depend on patient factors, the jet nebulizer utilized, and compressor performance. Using the Pari-LC-Plus™ nebulizer (with face mask or mouthpiece) connected to a PRONEB™ compressor system, under in vitro conditions, the mean delivered dose from the mouth piece (% nominal dose) was approximately 46% of albuterol and 42% of ipratropium bromide at a mean flow rate of 3.6 L/min. The mean nebulization time was 15 minutes or less. Ipratropium Bromide and Albuterol Sulfate should be administered from jet nebulizers at adequate flow rates, via face masks or mouthpieces (see DOSAGE AND ADMINISTRATION).

CLINICAL PHARMACOLOGY

Ipratropium Bromide and Albuterol Sulfate Inhalation Solution is a combination of the β2-adrenergic bronchodilator, albuterol sulfate, and the anticholinergic bronchodilator, ipratropium bromide.

Albuterol sulfate Mechanism of Action

The prime action of β-adrenergic drugs is to stimulate adenyl cyclase, the enzyme that catalyzes the formation of cyclic-3’,5’-adenosine monophosphate (cAMP) from adenosine triphosphate (ATP). The cAMP thus formed mediates the cellular responses. In vitro studies and in vivo pharmacologic studies have demonstrated that albuterol has a preferential effect on β2-adrenergic receptors compared with isoproterenol. While it is recognized that β2-adrenergic receptors are the predominant receptors in bronchial smooth muscle, recent data indicated that 10% to 50% of the β-receptors in the human heart may be β2-receptors. The precise function of these receptors, however, is not yet established. Albuterol has been shown in most controlled clinical trials to have more effect on the respiratory tract, in the form of bronchial smooth muscle relaxation, than isoproterenol at comparable doses while producing fewer cardiovascular effects. Controlled clinical studies and other clinical experience have shown that inhaled albuterol, like other β-adrenergic agonist drugs, can produce a significant cardiovascular effect in some patients.

Pharmacokinetics

Albuterol sulfate is longer acting than isoproterenol in most patients by any route of administration, because it is not a substrate for the cellular uptake processes for catecholamine nor for the metabolism of catechol-O-methyl transferase. Instead the drug is conjugatively metabolized to albuterol 4’-O-sulfate.

Animal Pharmacology/Toxicology

Intravenous studies in rats with albuterol sulfate have demonstrated that albuterol crosses the blood-brain barrier and reaches brain concentrations amounting to approximately 5% of plasma concentrations. In structures outside of the blood-brain barrier (pineal and pituitary glands), albuterol concentrations were found to be 100 times those found in whole brain.

Studies in laboratory animals (minipigs, rodents, and dogs) have demonstrated the occurrence of cardiac arrythmias and sudden death (with histological evidence of myocardial necrosis) when beta-agonists and methyl-xanthines are administered concurrently. The clinical significance of these findings is unknown.

Ipratropium bromide Mechanism of Action

Ipratropium bromide is an anticholinergic (parasympatholytic) agent, which blocks the muscarinic receptors of acetylcholine, and, based on animal studies, appears to inhibit vagally mediated reflexes by antagonizing the action of acetylcholine, the transmitter agent released from the vagus nerve. Anticholinergics prevent the increases in intracellular concentration of cyclic guanosine monophosphate (cGMP), resulting from the interaction of acetylcholine with the muscarinic receptors of bronchial smooth muscle.

Pharmacokinetics

The bronchodilation following inhalation of ipratropium is primarily a local, site-specific effect, not a systemic one. Much of an inhaled dose is swallowed as shown by fecal excretion studies. Following nebulization of a 1-mg dose to healthy volunteers, a mean of 4% of the dose was excreted unchanged in the urine.

Ipratropium bromide is minimally (0% to 9% in vitro) bound to plasma albumin and α1-acid glycoproteins. It is partially metabolized to inactive ester hydrolysis products. Following intravenous administration, approximately one-half is excreted unchanged in the urine. The half-life of elimination is about 1.6 hours after intravenous administration. Ipratropium bromide that reaches the systemic circulation is reportedly removed by the kidneys rapidly at a rate that exceeds the glomerular filtration rate. The pharmacokinetics of Ipratropium Bromide and Albuterol Sulfate Inhalation Solution or ipratropium bromide have not been studied in the elderly and in patients with hepatic or renal insufficiency (see PRECAUTIONS).

Animal Pharmacology/Toxicology

Autoradiographic studies in rats have shown that ipratropium does not penetrate the blood-brain barrier.

Ipratropium Bromide 0.5 mg and Albuterol Sulfate 3.0 mg Mechanism of Action

Ipratropium Bromide and Albuterol Sulfate is expected to maximize the response to treatment in patients with chronic obstructive pulmonary disease (COPD) by reducing bronchospasm through two distinctly different mechanisms: sympathomimetic (albuterol sulfate) and anticholinergic/parasympatholytic (ipratropium bromide). Simultaneous administration of both an anticholinergic and a ß2-sympathomimetic is designed to produce greater bronchodilation effects than when either drug is utilized alone at its recommended dosage.

Animal Pharmacology/Toxicology

In 30-day studies in Sprague-Dawley rats and Beagle dogs, subcutaneous doses of up to 205.5 mcg/kg of ipratropium administered with up to 1000 mcg/kg albuterol in rats and 3.16 mcg/kg ipratropium and 15 mcg/kg albuterol in dogs (less than the maximum recommended daily inhalation dose for adults on a mg/m^2 basis) did not cause death or potentiation of the cardiotoxicity induced by albuterol administered alone.

Pharmacokinetics

In a double blind, double period, crossover study, 15 male and female subjects were administered single doses of Ipratropium Bromide and Albuterol Sulfate or albuterol sulfate inhalation solution at two times the recommended single doses as two inhalations separated by 15 minutes. The total nebulized dose of albuterol sulfate from both treatments was 6.0 mg and the total dose of ipratropium bromide from Ipratropium Bromide and Albuterol Sulfate was 1.0 mg. Peak albuterol plasma concentrations occurred at 0.8 hours after dosing for both treatments. The mean peak albuterol concentration following administration of albuterol sulfate alone was 4.86 (± 2.65) mg/mL and it was 4.65 (± 2.92) mg/mL for Ipratropium Bromide and Albuterol Sulfate. Mean AUC values for the two treatments were 26.6 (± 15.2) ng•hr/mL (albuterol sulfate alone) versus 24.2 (± 14.5) ng•hr/mL (Ipratropium Bromide and Albuterol Sulfate). The mean t1/2 values were 7.2 (± 1.3) hours (albuterol sulfate alone) and 6.7 (± 1.7) hours (Ipratropium Bromide and Albuterol Sulfate). A mean of 8.4 (± 8.9)% of the albuterol dose was excreted unchanged in urine following administration of two vials of Ipratropium Bromide and Albuterol Sulfate which is similar to 8.8 (± 7.3)% that was obtained from albuterol sulfate inhalation solution. There were no statistically significant differences in the pharmacokinetics of albuterol between the two treatments. For ipratropium, a mean of 3.9 (± 5.1)% of the ipratropium bromide dose was excreted unchanged in urine following two vials of Ipratropium Bromide and Albuterol Sulfate Inhalation Solution, which is comparable with previously reported data.

Clinical Trials

In a 12 week, randomized, double-blind, positive-control, crossover study of albuterol sulfate, ipratropium bromide, and Ipratropium Bromide and Albuterol Sulfate, 863 COPD patients were evaluated for bronchodilator efficacy comparing Ipratropium Bromide and Albuterol Sulfate with albuterol sulfate and ipratropium bromide alone.

Ipratropium Bromide and Albuterol Sulfate demonstrated significantly better changes in FEV1, as measured from baseline to peak response, when compared with either albuterol sulfate or ipratropium bromide. Ipratropium Bromide and Albuterol Sulfate was also shown to have the rapid onset associated with albuterol sulfate, with a mean time to peak FEV1 of 1.5 hours, and the extended duration associated with ipratropium bromide with a duration of 15% response in FEV1 of 4.3 hours.

Figure 3.1-3. Mean Change in FEV1 - Measured on Day 14

This study demonstrated that each component of Ipratropium Bromide and Albuterol Sulfate contributed to the improvement in pulmonary function, especially during the first 4 to 5 hours after dosing, and that Ipratropium Bromide and Albuterol Sulfate was significantly more effective than albuterol sulfate or ipratropium bromide alone.

INDICATIONS AND USAGE

Ipratropium Bromide and Albuterol Sulfate is indicated for the treatment of bronchospasm associated with COPD in patients requiring more than one bronchodilator.

CONTRAINDICATIONS

Ipratropium Bromide and Albuterol Sulfate is contraindicated in patients with a history of hypersensitivity to any of its components, or to atropine and its derivatives.

WARNINGS

Paradoxical Bronchospasm

In the clinical study of Ipratropium Bromide and Albuterol Sulfate, paradoxical bronchospasm was not observed. However, paradoxical bronchospasm has been observed with both inhaled ipratropium bromide and albuterol products and can be life-threatening. If this occurs, Ipratropium Bromide and Albuterol Sulfate should be discontinued immediately and alternative therapy instituted.

Do Not Exceed Recommended Dose

Fatalities have been reported in association with excessive use of inhaled products containing sympathomimetic amines and with the home use of nebulizers.

Cardiovascular Effect

Ipratropium Bromide and Albuterol Sulfate, like other beta adrenergic agonists, can produce a clinically significant cardiovascular effect in some patients as measured by pulse rate, blood pressure, and/or symptoms. Although such effects are uncommon for Ipratropium Bromide and Albuterol Sulfate at recommended doses, if they occur, the drug may need to be discontinued. In addition, beta agonists have been reported to produce ECG changes, such as flattening of the T-wave, prolongation of the QTc interval, and ST segment depression. The clinical significance of these findings is unknown. Therefore, Ipratropium Bromide and Albuterol Sulfate, like other sympathomimetic amines, should be used with caution in patients with cardiovascular disorders, especially coronary insufficiency, cardiac arrhythmias, and hypertension.

Immediate Hypersensitivity Reactions

Immediate hypersensitivity reactions to albuterol and/or ipratropium bromide may occur after the administration of Ipratropium Bromide and Albuterol Sulfate as demonstrated by rare cases of urticaria, angioedema, rash, pruritus, oropharyngeal edema, bronchospasm, and anaphylaxis.

PRECAUTIONS

General 1. Effects Seen with Sympathomimetic Drugs

As with all products containing sympathomimetic amines, Ipratropium Bromide and Albuterol Sulfate should be used with caution in patients with cardiovascular disorders, especially coronary insufficiency, cardiac arrhythmias, and hypertension; in patients with convulsive disorders, hyperthyroidism, or diabetes mellitus; and in patients who are unusually responsive to sympathomimetic amines. Large doses of intravenous albuterol have been reported to aggravate pre-existing diabetes mellitus and ketoacidosis. Additionally, β-agonists may cause a decrease in serum potassium in some patients, possibly through intracellular shunting. The decrease is usually transient, not requiring supplementation.

2. Effects Seen with Anticholinergic Drugs

Due to the presence of ipratropium bromide in Ipratropium Bromide and Albuterol Sulfate, it should be used with caution in patients with narrow-angle glaucoma, prostatic hypertrophy, or bladder-neck obstruction.

3. Use in Hepatic or Renal Diseases

Ipratropium Bromide and Albuterol Sulfate has not been studied in patients with hepatic or renal insufficiency. It should be used with caution in these patient populations.

Information for Patients

The action of Ipratropium Bromide and Albuterol Sulfate should last up to 5 hours. Ipratropium Bromide and Albuterol Sulfate should not be used more frequently than recommended. Patients should be instructed not to increase the dose or frequency of Ipratropium Bromide and Albuterol Sulfate without consulting their healthcare provider. If symptoms worsen, patients should be instructed to seek medical consultation.

Patients must avoid exposing their eyes to this product as temporary papillary dilation, blurred vision, eye pain, or precipitation or worsening of narrow-angle glaucoma may occur, and therefore proper nebulizer technique should be assured, particularly if a mask is used.

If a patient becomes pregnant or begins nursing while on Ipratropium Bromide and Albuterol Sulfate, they should contact their healthcare provider about use of Ipratropium Bromide and Albuterol Sulfate.

See the illustrated Patient’s Instruction for Use in the product package insert.

Drug Interactions Anticholinergic agents

Although ipratropium bromide is minimally absorbed into the systemic circulation, there is some potential for an additive interaction with concomitantly used anticholinergic medications. Caution is, therefore, advised in the co-administration of Ipratropium Bromide and Albuterol Sulfate with other drugs having anticholinergic properties.

ß-adrenergic agents

Caution is advised in the co-administration of Ipratropium Bromide and Albuterol Sulfate and other sympathomimetic agents due to the increased risk of adverse cardiovascular effects.

ß-receptor blocking agents

These agents and albuterol sulfate inhibit the effect of each other. β-receptor blocking agents should be used with caution in patients with hyperreactive airways, and if used, relatively selective ß1 selective agents are recommended.

Diuretics

The electrocardiogram (ECG) changes and/or hypokalemia that may result from the administration of non-potassium sparing diuretics (such as loop or thiazide diuretics) can be acutely worsened by β-agonists, especially when the recommended dose of the β-agonist is exceeded. Although the clinical significance of these effects is not known, caution is advised in the co-administration of β-agonist-containing drugs, such as Ipratropium Bromide and Albuterol Sulfate, with non-potassium sparing diuretics.

Monoamine oxidase inhibitors or tricyclic antidepressants

Ipratropium Bromide and Albuterol Sulfate should be administered with extreme caution to patients being treated with monoamine oxidase inhibitors or tricyclic antidepressants, or within 2 weeks of discontinuation of such agents because the action of albuterol sulfate on the cardiovascular system may be potentiated.

Carcinogenesis, Mutagenesis, Impairment of Fertility Albuterol Sulfate

In a 2-year study in Sprague-Dawley rats, albuterol sulfate caused a significant dose-related increase in the incidence of benign leiomyomas of the mesovarium at and above dietary doses of 2 mg/kg (approximately equal to the maximum recommended daily inhalation dose for adults on a mg/m^2 basis). In another study, this effect was blocked by the coadministration of propranolol, a non-selective beta-adrenergic antagonist.

In an 18-month study in CD-1 mice, albuterol sulfate showed no evidence of tumorigenicity at dietary doses up to 500mg/kg (approximately 140 times the maximum recommended daily inhalation dose for adults on a mg/m^2 basis). In a 22-month study in Golden hamsters, albuterol sulfate showed no evidence of tumorigenicity at dietary doses up to 50 mg/kg (approximately 20 times the maximum recommended daily inhalation dose for adults on a mg/m^2 basis).

Albuterol sulfate was not mutagenic in the Ames test or a mutation test in yeast. Albuterol sulfate was not clastogenic in a human peripheral lymphocyte assay or in an AH1 strain mouse micronucleous assay.

Reproduction studies in rats demonstrated no evidence of impaired fertility at oral doses of albuterol sulfate up to 50 mg/kg (approximately 25 times the maximum recommended daily inhalation dose for adults on a mg/m^2 basis).

Ipratropium bromide

In 2-year studies in Sprague-Dawley rats and CD-1 mice, ipratropium bromide showed no evidence of tumorigenicity at oral doses up to 6 mg/kg (approximately 15 times and 8 times the maximum recommended daily inhalation dose for adults in rats and mice respectively, on a mg/m^2 basis).

Ipratropium bromide was not mutagenic in the Ames test and mouse dominant lethal test. Ipratropium bromide was not clastogenic in a mouse micronucleous assay.

A reproduction study in rats demonstrated decreased conception and increased resorptions when ipratropium bromide was administered orally at a dose of 90 mg/kg (approximately 240 times the maximum recommended daily inhalation dose for adults on a mg/m^2 basis). These effects were not seen with a dose of 50 mg/kg (approximately 140 times the maximum recommended daily inhalation dose for adults on a mg/m^2 basis).

Pregnancy TERATOGENIC EFFECTS: Pregnancy Category CAlbuterol sulfate Pregnancy Category C

Albuterol sulfate has been shown to be teratogenic in mice. A study in CD-1 mice given albuterol sulfate subcutaneously showed cleft palate formation in 5 of 111 (4.5%) fetuses at 0.25 mg/kg (less than the maximum recommended daily inhalation dose for adults on a mg/m^2 basis) and in 10 of 108 (9.3%) fetuses at 2.5 mg/kg (approximately equal to the maximum recommended daily inhalation dose for adults on a mg/m^2 basis). The drug did not induce cleft palate formation when administered subcutaneously at a dose of 0.025 mg/kg (less than the maximum recommended daily inhalation dose for adults on a mg/m^2 basis). Cleft palate formation also occurred in 22 of 72 (30.5%) fetuses from females treated subcutaneously with 2.5 mg/kg isoproterenol (positive control).

A reproduction study in Stride rabbits revealed cranioschisis in 7 of 19 (37%) fetuses when albuterol was administered orally at a dose of 50 mg/kg (approximately 55 times the maximum recommended daily inhalation dose for adults on a mg/m^2 basis).

A study in which pregnant rats were dosed with radiolabeled albuterol sulfate demonstrated that drug-related material is transferred from the maternal circulation to the fetus.

During worldwide marketing experience, various congenital anomalies, including cleft palate and limb defects, have been reported in the offspring of patients being treated with albuterol. Some of the mothers were taking multiple medications during their pregnancies. Because no consistent pattern of defects can be discerned, a relationship between albuterol use and congenital anomalies has not been established.

Ipratropium bromide Pregnancy Category B

Reproduction studies in CD-1 mice, Sprague-Dawley rats and New Zealand rabbits demonstrated no evidence of teratogenicity at oral doses up to 10, 100, and 125 mg/kg, respectively (approximately 15, 270, and 680 times the maximum recommended daily inhalation dose for adults on a mg/m^2 basis). Reproduction studies in rats and rabbits demonstrated no evidence of teratogenicity at inhalation doses up to 1.5 and 1.8 mg/kg, respectively (approximately 4 and 10 times the maximum recommended daily inhalation dose for adults on a mg/m^2 basis). There are no adequate and well-controlled studies of the use of Ipratropium Bromide and Albuterol Sulfate, albuterol sulfate, or ipratropium bromide in pregnant women. Ipratropium Bromide and Albuterol Sulfate should be used during pregnancy only if the potential benefit justifies the potential risk to the fetus.

Labor and Delivery

Oral albuterol sulfate has been shown to delay preterm labor in some reports. Because of the potential of albuterol to interfere with uterine contractility, use of Ipratropium Bromide and Albuterol Sulfate during labor should be restricted to those patients in whom the benefits clearly outweigh the risks.

Nursing Mothers

It is not known whether the components of Ipratropium Bromide and Albuterol Sulfate are excreted in human milk. Although lipidinsoluble quaternary bases pass into breast milk, it is unlikely that ipratropium bromide would reach the infant to an important extent, especially when taken as a nebulized solution. Because of the potential for tumorigenicity shown for albuterol sulfate in some animals, a decision should be made whether to discontinue nursing or discontinue Ipratropium Bromide and Albuterol Sulfate, taking into account the importance of the drug to the mother.

Pediatric Use

The safety and effectiveness of Ipratropium Bromide and Albuterol Sulfate in patients below 18 years of age have not been established.

Geriatric Use

Of the total number of subjects in clinical studies of Ipratropium Bromide and Albuterol Sulfate, 62 percent were 65 and over, while 19 percent were 75 and over. No overall differences in safety or effectiveness were observed between these subjects and younger subjects, and other reported clinical experience has not identified differences in responses between the elderly and younger patients, but greater sensitivity of some older individuals cannot be ruled out.

ADVERSE REACTIONS

Adverse reaction information concerning Ipratropium Bromide and Albuterol Sulfate was derived from the 12-week controlled clinical trial.

ADVERSE EVENTS OCCURRING IN ≥ 1% OF ≥ 1 TREATMENT GROUP(S) AND WHERE THE COMBINATION TREATMENT SHOWED THE HIGHEST PERCENTAGE
Body System COSTART Term | Albuterol n (%) | Ipratropium n (%) | Ipratropium Bromide and Albuterol Sulfate n (%)
NUMBER OF PATIENTS | 761 | 754 | 765
N (%) Patients with AE | 327 (43.0) | 329 (43.6) | 367 (48.0)
BODY AS A WHOLE
Pain | 8 (1.1) | 4 (0.5) | 10 (1.3)
Pain chest | 11 (1.4) | 14 (1.9) | 20 (2.6)
DIGESTIVE
Diarrhea | 5 (0.7) | 9 (1.2) | 14 (1.8)
Dyspepsia | 7 (0.9) | 8 (1.1) | 10 (1.3)
Nausea | 7 (0.9) | 6 (0.8) | 11 (1.4)
MUSCULO-SKELETAL
Cramps leg | 8 (1.1) | 6 (0.8) | 11 (1.4)
RESPIRATORY
Bronchitis | 11 (1.4) | 13 (1.7) | 13 (1.7)
Lung Disease | 36 (4.7) | 34 (4.5) | 49 (6.4)
Pharyngitis | 27 (3.5) | 27 (3.6) | 34 (4.4)
Pneumonia | 7 (0.9) | 8 (1.1) | 10 (1.3)
UROGENITAL
Infection urinary tract | 3 (0.4) | 9 (1.2) | 12 (1.6)

Additional adverse reactions reported in more than 1% of patients treated with Ipratropium Bromide and Albuterol Sulfate included constipation and voice alterations.

In the clinical trial, there was a 0.3% incidence of possible allergic-type reactions, including skin rash, pruritus, and urticaria.

Additional information derived from the published literature on the use of albuterol sulfate and ipratropium bromide singly or in combination includes precipitation or worsening of narrow-angle glaucoma, acute eye pain, blurred vision, paradoxical bronchospasm, wheezing, exacerbation of COPD symptoms, drowsiness, aching, flushing, upper respiratory tract infection, palpitations, taste perversion, elevated heart rate, sinusitis, back pain and sore throat.

OVERDOSAGE

The effects of overdosage with Ipratropium Bromide and Albuterol Sulfate are expected to be related primarily to albuterol sulfate, since ipratropium bromide is not well-absorbed systemically after oral or aerosol administration. The expected symptoms with overdosage are those of excessive beta-adrenergic stimulation and/or occurrence or exaggeration of symptoms such as seizures, angina, hypertension or hypotension, tachycardia with rates up to 200 beats per minute, arrhythmia, nervousness, headache, tremor, dry mouth, palpitation, nausea, dizziness, fatigue, malaise, insomnia, and exaggeration of pharmacological effects listed in ADVERSE REACTIONS. Hypokalemia may also occur. As with all sympathomimetic aerosol medications, cardiac arrest and even death may be associated with abuse of Ipratropium Bromide and Albuterol Sulfate. Treatment consists of discontinuation of Ipratropium Bromide and Albuterol Sulfate together with appropriate symptomatic therapy. The judicious use of a cardioselective beta-receptor blocker may be considered, bearing in mind that such medication can produce bronchospasm. There is insufficient evidence to determine if dialysis is beneficial for overdosage of Ipratropium Bromide and Albuterol Sulfate.

The oral median lethal dose of albuterol sulfate in mice is greater than 2000 mg/kg (approximately 540 times the maximum recommended daily inhalation dose of Ipratropium Bromide and Albuterol Sulfate on a mg/m^2 basis). The subcutaneous median lethal dose of albuterol sulfate in mature rats and small young rats is approximately 450 and 2000 mg/kg respectively (approximately 240 and 1100 times the maximum recommended daily inhalation dose of Ipratropium Bromide and Albuterol Sulfate on a mg/m^2 basis, respectively). The inhalation median lethal dose has not been determined in animals. The oral median lethal dose of ipratropium bromide in mice, rats and dogs is greater than 1000 mg/kg, approximately 1700 mg/kg and approximately 400 mg/kg, respectively (approximately 1400, 4600, and 3600 times the maximum recommended daily inhalation dose in adults on a mg/m^2 basis, respectively).

DOSAGE AND ADMINISTRATION

The recommended dose of Ipratropium Bromide and Albuterol Sulfate is one 3 mL vial administered 4 times per day via nebulization with up to 2 additional 3 mL doses allowed per day, if needed. Safety and efficacy of additional doses or increased frequency of administration of Ipratropium Bromide and Albuterol Sulfate beyond these guidelines has not been studied and the safety and efficacy of extra doses of albuterol sulfate or ipratropium bromide in addition to the recommended doses of Ipratropium Bromide and Albuterol Sulfate have not been studied.

The use of Ipratropium Bromide and Albuterol Sulfate can be continued as medically indicated to control recurring bouts of bronchospasm. If a previously effective regimen fails to provide the usual relief, medical advice should be sought immediately, as this is often a sign of worsening COPD, which would require reassessment of therapy.

A Pari-LC-Plus™ nebulizer (with face mask or mouthpiece) connected to a PRONEB™ compressor was used to deliver Ipratropium Bromide and Albuterol Sulfate to each patient in one U.S. clinical study. The safety and efficacy of Ipratropium Bromide and Albuterol Sulfate delivered by other nebulizers and compressors have not been established.

Ipratropium Bromide and Albuterol Sulfate should be administered via jet nebulizer connected to an air compressor with an adequate air flow, equipped with a mouthpiece or suitable face mask.

HOW SUPPLIED

Ipratropium Bromide 0.5 mg and Albuterol Sulfate 3.0 mg is supplied as a 3-mL sterile solution for nebulization in sterile low-density polyethylene unit-dose vials. Store in pouch until time of use. Supplied in cartons as listed below.

NDC 54868-5974-0 30 vials per carton/5 vials per foil pouch

Store between 2°C and 25°C (36°F and 77°F). Protect from light.

Manufactured By
Dey, L.P.
Napa, CA 94558
for
Sandoz Inc., Princeton, NJ 08540

03-738-02
Feb. 09

Relabeling of "Additional Barcode Label" by:
Physicians Total Care, Inc.
Tulsa, OK 74146

Patient Information
Ipratropium Bromide 0.5 mg and Albuterol Sulfate 3.0 mg* Inhalation Solution
*Equivalent to 2.5 mg albuterol base

Prescription Only.

Read the patient information that comes with Ipratropium Bromide 0.5 mg and Albuterol Sulfate 3.0 mg before you start using it and each time you get a refill. There may be new information. This leaflet does not take the place of talking with your doctor about your medical condition or your treatment.

What is Ipratropium Bromide 0.5 mg and Albuterol Sulfate 3.0 mg?

Ipratropium Bromide 0.5 mg and Albuterol Sulfate 3.0 mg is a combination of two medicines called bronchodilators. Ipratropium Bromide 0.5 mg and Albuterol Sulfate 3.0 mg contains albuterol sulfate, which is a beta-adrenergic agonist, and ipratropium bromide, which is an anticholinergic. These two medicines work together to help open the airways in your lungs. Ipratropium Bromide 0.5 mg and Albuterol Sulfate 3.0 mg is used to help treat airway narrowing (bronchospasm) that happens with chronic obstructive pulmonary disease (COPD) in adult patients who need to use more than one bronchodilator medicine.

Who should not use Ipratropium Bromide 0.5 mg and Albuterol Sulfate 3.0 mg?

Do not use Ipratropium Bromide 0.5 mg and Albuterol Sulfate 3.0 mg if you: Are allergic to any of the ingredients in Ipratropium Bromide and Albuterol Sulfate or to atropine. The active ingredients are albuterol sulfate and ipratropium bromide. See the end of this leaflet for a complete list of ingredients in Ipratropium Bromide 0.5 mg and Albuterol Sulfate 3.0 mg.

Ipratropium Bromide 0.5 mg and Albuterol Sulfate 3.0 mg has not been studied in patients younger than 18 years of age.

What should I tell my doctor before I start using Ipratropium Bromide 0.5 mg and Albuterol Sulfate 3.0 mg?

Tell your doctor about all of your conditions, including if you:

- Have heart problems. This includes coronary artery disease and heart rhythm problems.
- Have high blood pressure
- Have diabetes
- Have or had seizures
- Have a thyroid problem called hyperthyroidism
- Have an eye problem called narrow-angle glaucoma
- Have liver or kidney problems
- Have problems urinating due to bladder-neck blockage or an enlarged prostate (men)
- Are pregnant or planning to become pregnant. It is not known if Ipratropium Bromide 0.5 mg and Albuterol Sulfate 3.0 mg can harm your unborn baby. You and your doctor will have to decide if Ipratropium Bromide 0.5 mg and Albuterol Sulfate 3.0 mg is right for you during a pregnancy.
- Are breastfeeding. It is not known if Ipratropium Bromide 0.5 mg and Albuterol Sulfate 3.0 mg passes into your milk or if it can harm your baby. You and your doctor should decide whether you should take Ipratropium Bromide 0.5 mg and Albuterol Sulfate 3.0 mg or breastfeed, but not both.

Tell your doctor about all the medicines you take including prescription and non-prescription medicines, vitamins and herbal supplements. Ipratropium Bromide 0.5 mg and Albuterol Sulfate 3.0 mg and other medicines can interact. This may cause serious side effects. Especially tell your doctor if you take:

- Other medicines that contain anticholinergics such as ipratropium bromide. This also includes medicines used for Parkinson’s disease.
- Other medicines that contain beta-agonists such as albuterol sulfate. These are usually used to treat airway narrowing (bronchospasm).
- Medicines called beta-blockers. These are usually used for high blood pressure or heart problems.
- Medicines called “water pills” (diuretics)
- Medicines for depression called monoamine oxidase inhibitors (MAOIs) or tricyclic antidepressants.

Ask your doctor or pharmacist if you are not sure if you take any of these types of medicines. Know the medicines you take. Keep a list of them and show it to your doctor and pharmacists when you get a new medicine.

How should I use Ipratropium Bromide 0.5 mg and Albuterol Sulfate 3.0 mg?

- Read the Patient’s Instructions for Use that you get with your prescription. Talk to your doctor or pharmacist if you have any questions.
- Take Ipratropium Bromide 0.5 mg and Albuterol Sulfate 3.0 mg exactly as prescribed by your doctor. Do not change your dose or how often you use Ipratropium Bromide 0.5 mg and Albuterol Sulfate 3.0 mg without talking to your doctor. Inhale Ipratropium Bromide 0.5 mg and Albuterol Sulfate 3.0 mg through your mouth and into your lungs using a machine called a nebulizer.
- Ipratropium Bromide 0.5 mg and Albuterol Sulfate 3.0 mg may help to open your airways for up to 5 hours after taking this medicine. If Ipratropium Bromide 0.5 mg and Albuterol Sulfate 3.0 mg does not help your airway narrowing (bronchospasm) or your bronchospasm gets worse, call your doctor right away or get emergency help if needed.

What should I avoid while using Ipratropium Bromide 0.5 mg and Albuterol Sulfate 3.0 mg?

Do not get Ipratropium Bromide 0.5 mg and Albuterol Sulfate 3.0 mg in your eyes.

Be careful not to spray Ipratropium Bromide 0.5 mg and Albuterol Sulfate 3.0 mg in your eyes while you are using your nebulizer. Ipratropium Bromide 0.5 mg and Albuterol Sulfate 3.0 mg can cause the following short-term eye problems:

- Enlarged pupils
- Blurry vision
- Eye pain

Ipratropium Bromide 0.5 mg and Albuterol Sulfate 3.0 mg can cause a serious eye problem called narrow-angle glaucoma or worsen the narrow-angle glaucoma you already have.

What are the possible side effects with Ipratropium Bromide 0.5 mg and Albuterol Sulfate 3.0 mg?

Ipratropium Bromide 0.5 mg and Albuterol Sulfate 3.0 mg may cause the following serious side effects:

- Worsening of the narrowing in your airways (bronchospasm). This side effect can be life-threatening and has happened with both of the medicines that are in Ipratropium Bromide 0.5 mg and Albuterol Sulfate 3.0 mg. Stop Ipratropium Bromide 0.5 mg and Albuterol Sulfate 3.0 mg and call your doctor right away or get emergency help if your breathing problems get worse while or after using Ipratropium Bromide 0.5 mg and Albuterol Sulfate 3.0 mg.
- Serious and life-threatening allergic reactions. Symptoms of a serious allergic reaction include:
  - Hives, rash
  - Swelling of your face, eyelids, lips, tongue, or throat, and trouble swallowing
  - Worsening of your breathing problems such as wheezing, chest tightness or shortness of breath
  - Shock (loss of blood pressure and consciousness)

The most common side effects with Ipratropium Bromide 0.5 mg and Albuterol Sulfate 3.0 mg include lung disease, sore throat, chest pain, constipation, diarrhea, bronchitis, urinary tract infection, leg cramps, nausea, upset stomach, voice changes, and pain. These are not all the side effects with Ipratropium Bromide 0.5 mg and Albuterol Sulfate 3.0 mg. For a complete list, ask your doctor or pharmacist.

How should I store Ipratropium Bromide 0.5 mg and Albuterol Sulfate 3.0 mg?

- Store Ipratropium Bromide 0.5 mg and Albuterol Sulfate 3.0 mg between 36° and 77°F (2° and 25°C). Protect from light. Keep the unused vials in the foil pouch or carton.
- Safely discard Ipratropium Bromide 0.5 mg and Albuterol Sulfate 3.0 mg that is out-of-date or no longer needed.
- Keep Ipratropium Bromide 0.5 mg and Albuterol Sulfate 3.0 mg and all medicines out of the reach of children.

General advice about Ipratropium Bromide 0.5 mg and Albuterol Sulfate 3.0 mg

Medicines are sometimes prescribed for conditions that are not mentioned in the patient information leaflets. Do not use Ipratropium Bromide 0.5 mg and Albuterol Sulfate 3.0 mg for a condition for which it was not prescribed. Do not give Ipratropium Bromide 0.5 mg and Albuterol Sulfate 3.0 mg to other people, even if they have the same symptoms you have. It may harm them.

This leaflet summarizes the most important information about Ipratropium Bromide 0.5 mg and Albuterol Sulfate 3.0 mg. If you would like more information, talk with your doctor. You can ask your doctor or pharmacist for information about Ipratropium Bromide 0.5 mg and Albuterol Sulfate 3.0 mg that is written for health professionals.

What are the ingredients in Ipratropium Bromide 0.5 mg and Albuterol Sulfate 3.0 mg?

Active Ingredients: ipratropium bromide and albuterol sulfate

Inactive Ingredients: sodium chloride, hydrochloric acid, and edetate sodium, USP.

Ipratropium Bromide 0.5 mg and Albuterol Sulfate 3.0 mg*Inhalation Solution
*Equivalent to 2.5 mg albuterol base

Patient’s Instructions for Use

Read this patient information completely every time your prescription is filled as information may have changed. Keep these instructions with your medication as you may want to read them again.

Ipratropium Bromide and Albuterol Sulfate should only be used under the direction of a physician. Your physician and pharmacist have more information about Ipratropium Bromide and Albuterol Sulfate and the condition for which it has been prescribed. Contact them if you have additional questions.

Storing your Medicine

Store Ipratropium Bromide and Albuterol Sulfate between 2°C and 25°C (36°F and 77°F). Vials should be protected from light before use, therefore, keep unused vials in the foil pouch or carton. Do not use after the expiration (EXP) date printed on the carton.

Dose

Ipratropium Bromide and Albuterol Sulfate is supplied as a single-dose, ready-to-use vial containing 3 mL of solution. No mixing or dilution is needed. Use one new vial for each nebulizer treatment.

FOLLOW THESE DIRECTIONS FOR USE OF YOUR NEBULIZER/COMPRESSOR OR THE DIRECTIONS GIVEN BY YOUR HEALTHCARE PROVIDER. A TYPICAL EXAMPLE IS SHOWN BELOW.

Instructions for Use

- Remove one vial from the foil pouch. Place remaining vials back into pouch for storage.
- Twist the cap completely off the vial and squeeze the contents into the nebulizer reservoir (Figure 1).

- Connect the nebulizer to the mouthpiece or face mask (Figure 2).

- Connect the nebulizer to the compressor.
- Sit in a comfortable, upright position; place the mouthpiece in your mouth (Figure 3) or put on the face mask (Figure 4); and turn on the compressor.

- Breathe as calmly, deeply and evenly as possible through your mouth until no more mist is formed in the nebulizer chamber (about 5-15 minutes). At this point, the treatment is finished.
- Clean the nebulizer (see manufacturer’s instructions).

Manufactured By Dey, L.P.
Napa, CA 94558 for
Sandoz Inc., Princeton, NJ 08540

03-738-02

PACKAGE LABEL

PRINCIPAL DISPLAY PANEL - 0.5 mg Ipratropium Bromide and 3.0 mg Albuterol Sulfate

Ipratropium Bromide
0.5 mg and
Albuterol Sulfate
3.0 mg

INHALATION SOLUTION

Sterile Unit-Dose Vials For Inhalation Only

Carton contains: 6 pouches of 5-3 mL vials each

Vial contains:
0.5 mg ipratropium bromide
3.0 mg albuterol sulfate*
*Equivalent to 2.5 mg albuterol base.

Rx only

INGREDIENTS:

Active: 0.5 mg ipratropium bromide and 3.0 mg
albuterol sulfate*.

Inactive: Sodium chloride, edetate disodium, and
hydrochloric acid (to adjust to pH 4) and purified water.

*Equivalent to 2.5 mg albuterol base.

STORAGE CONDITIONS: PROTECT FROM LIGHT.
STORE IN POUCH UNTIL TIME OF USE. Store between
2°C and 25°C (36°F and 77°F).

USUAL DOSAGE: See accompanying prescribing infor-
mation. USE ONLY AS DIRECTED BY YOUR PHYSI-
CIAN. DO NOT EXCEED RECOMMENDED DOSAGE.

KEEP OUT OF REACH OF CHILDREN.

Rev. 02-2009